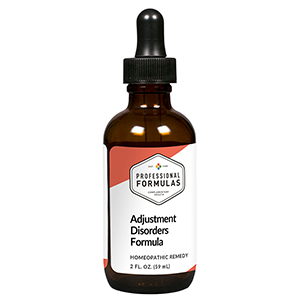 DRUG LABEL: Adjustment Disorders Formula
NDC: 63083-2097 | Form: LIQUID
Manufacturer: Professional Complementary Health Formulas
Category: homeopathic | Type: HUMAN OTC DRUG LABEL
Date: 20190815

ACTIVE INGREDIENTS: DIEFFENBACHIA SEGUINE WHOLE 3 [hp_X]/59 mL; ANTIPYRINE 6 [hp_X]/59 mL; ARUNDO PLINIANA ROOT 6 [hp_X]/59 mL; DIGITALIS 6 [hp_X]/59 mL; NITROGLYCERIN 6 [hp_X]/59 mL; XEROPHYLLUM ASPHODELOIDES WHOLE 6 [hp_X]/59 mL; AGAVE ATROVIRENS TOP 12 [hp_X]/59 mL; WOOD CREOSOTE 24 [hp_X]/59 mL; LACHESIS MUTA VENOM 30 [hp_X]/59 mL; RABIES VIRUS 30 [hp_X]/59 mL
INACTIVE INGREDIENTS: ALCOHOL; WATER

C97

ACTIVE INGREDIENTS

Caladium seguinum 3X
Ustilago maydis 3X
Antipyrinum 6X
Arundo mauritanica 6X
Digitalis purpurea 6X
Glonoinum 6X
Xerophyllum asphodeloides 6X
Agave tequilana 12X
Kreosotum 24X
Lachesis mutus 30X
Lyssin 30X

QUESTIONS

Professional Formulas

PO Box 2034 Lake Oswego, OR 97035

INDICATIONS

For temporary relief of anxiousness, stress, or excessive worry or emotion.*

PURPOSE

*Claims based on traditional homeopathic practice, not accepted medical evidence. Not FDA evaluated.

WARNINGS

In case of overdose, get medical help or contact a poison control center right away.

Keep out of the reach of children.

PREGNANCY OR BREAST FEEDING

If pregnant or breastfeeding, ask a healthcare professional before use.

DIRECTIONS

Place drops under tongue 30 minutes before/after meals. Adults and children 12 years and over: Take 10 drops up to 3 times per day. Consult a physician for use in children under 12 years of age.

OTHER INFORMATION

Tamper resistant. If seal is broken, do not use. After opening, close container tightly and store at room temperature away from heat.

INACTIVE INGREDIENTS

20% ethanol, purified water.

LABEL

Est 1985

Professional Formulas

Complementary Health

Adjustment Disorders Formula

Homeopathic Remedy

2 FL. OZ. (59 mL)